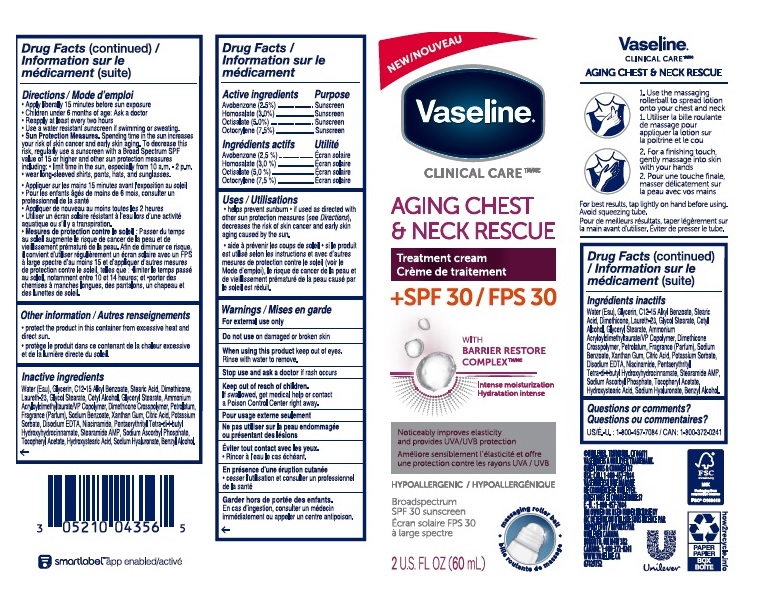 DRUG LABEL: Vaseline
NDC: 64942-1871 | Form: CREAM
Manufacturer: CONOPCO Inc. d/b/a Unilever
Category: otc | Type: HUMAN OTC DRUG LABEL
Date: 20241107

ACTIVE INGREDIENTS: OCTOCRYLENE 7.5 g/100 mL; OCTISALATE 5 g/100 mL; AVOBENZONE 2 g/100 mL; HOMOSALATE 3 g/100 mL
INACTIVE INGREDIENTS: GLYCOL STEARATE; WATER; NIACINAMIDE; CETYL ALCOHOL; XANTHAN GUM; ALKYL (C12-15) BENZOATE; AMMONIUM ACRYLOYLDIMETHYLTAURATE/VP COPOLYMER; .ALPHA.-TOCOPHEROL ACETATE; DIMETHICONE; SODIUM BENZOATE; GLYCERIN; 12-HYDROXYSTEARIC ACID; EDETATE DISODIUM ANHYDROUS; STEARAMIDE AMP; SODIUM ASCORBYL PHOSPHATE; POTASSIUM SORBATE; CITRIC ACID MONOHYDRATE; STEARIC ACID; PETROLATUM; DIMETHICONE CROSSPOLYMER (450000 MPA.S AT 12% IN CYCLOPENTASILOXANE); LAURETH-23; PENTAERYTHRITOL TETRAKIS(3-(3,5-DI-TERT-BUTYL-4-HYDROXYPHENYL)PROPIONATE); HYALURONATE SODIUM; GLYCERYL MONOSTEARATE; BENZYL ALCOHOL

Vaseline Aging Chest & Neck Rescue Treatment Cream SPF 30

Drug Facts

Active ingredient

Avobenzone (2.5%), Homosalate (3.0%), Octisalate (5%), Octocrylene (7.5%)

Purpose

Sunscreen

Uses

Helps prevent sunburn
If used as directed with other sun protection measeures (see Directions) decreases the risk of skin cancer and early skin aging caused by the sun

Warnings

For external use only
Do not use on damaged or broken skin
When using this product keep out of eyes. Rinse with water to remove
Stop use and ask a doctor if rash occurs

Keep out of reach of children
If product is swallowed, get medical help or contact a PoisonCcontrol Center right away.

Directions

Apply liberally 15 minutes before sun exposure
Children under 6 months of age: Ask a doctor.
Reapply at least every 2 hours
Use a water resistant sunscreen if swimming or sweating
Sun Protection Measures Spending time in the sun increases your risk of skin cancer and early skin aging. To decrease this rish, regularly use a sunscree with a Broad Spectum SPF value of 15 or higher and other sun protection measures including limit time in the sun,

- especially from 10a.m. - 2p.m.
- wear long-sleeved shirts, pants, hats and sunglasses

Inactive ingredients

Water (Eau), Glycerin, C12-15 Alkyl Benzoate, Stearic Acid, Dimethicone, Laureth-23, Glycol Stearate, Cetyl Alcohol, Glyceryl Stearate, Ammonium Acryloyldimethyltaurate/VP Copolymer, Dimethicone Crosspolymer, Petrolatum, Fragrance (Parfum), Sodium Benzoate, Xanthan Gum, Citric Acid, Potassium Sorbate, Disodium EDTA, Niacinamide, Pentaerythrityl Tetra-di-t-butyl Hydroxyhydrocinnamate, Stearamide AMP, Sodium Ascorbyl Phosphate, Tocopheryl Acetate, Hydroxystearic Acid, Sodium Hyaluronate, Benzyl Alcohol.

Questions or Comments?

1-800-457-7084